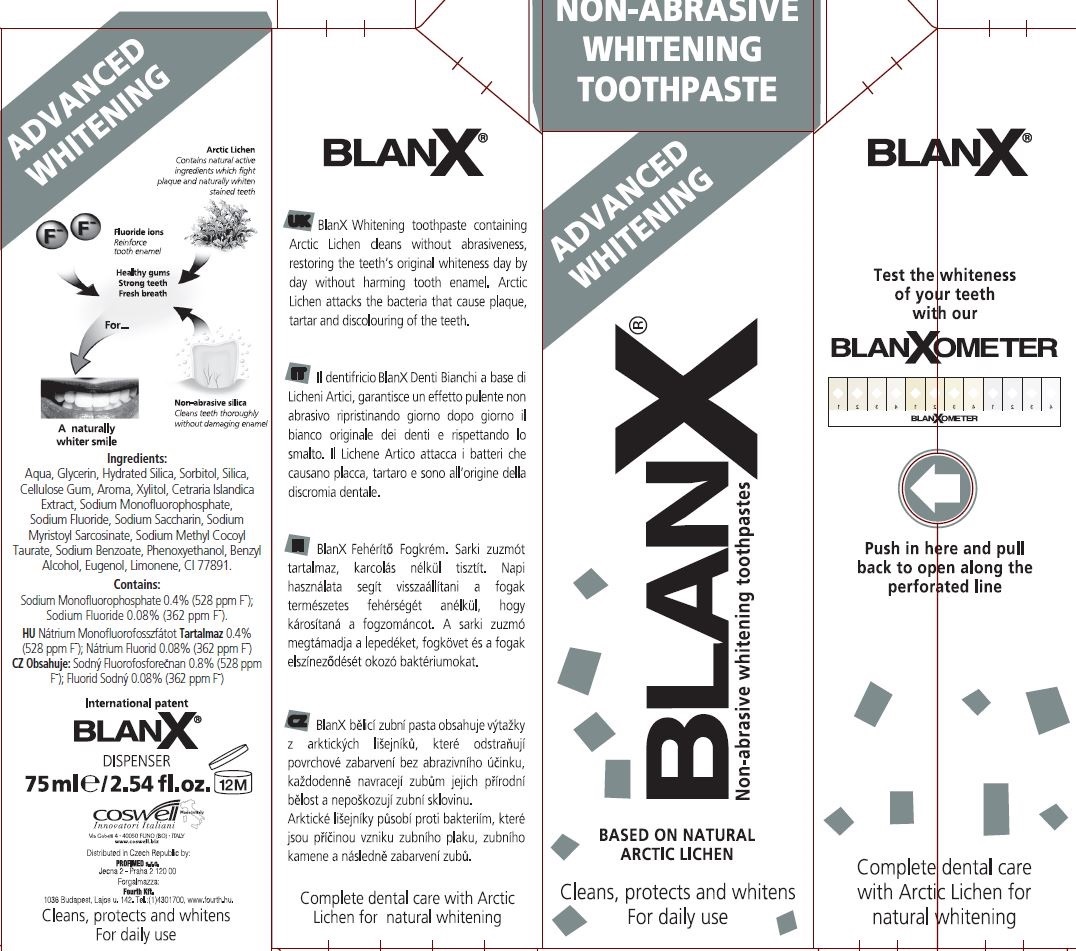 DRUG LABEL: BlanX Advanced Whitening
NDC: 70781-004 | Form: PASTE
Manufacturer: Coswell Spa
Category: otc | Type: HUMAN OTC DRUG LABEL
Date: 20190204

ACTIVE INGREDIENTS: SODIUM FLUORIDE 0.08 g/100 g; SODIUM MONOFLUOROPHOSPHATE 0.4 g/100 g
INACTIVE INGREDIENTS: SILICON DIOXIDE; SODIUM METHYL COCOYL TAURATE; XYLITOL; SODIUM MYRISTOYL SARCOSINATE; EUGENOL; LIMONENE, (+)-; TITANIUM DIOXIDE; BENZYL ALCOHOL; PHENOXYETHANOL; SACCHARIN SODIUM; SODIUM BENZOATE; CARBOXYMETHYLCELLULOSE SODIUM; GLYCERIN; CETRARIA ISLANDICA SUBSP. ISLANDICA; WATER; SORBITOL; HYDRATED SILICA

BlanX Advanced Whitening

ACTIVE INGREDIENT

Contains:

Sodium Monofluorophosphate 0.4% (528 ppm F)

Sodium Fluoride 0.08% (362 ppm F)

INACTIVE INGREDIENT

Ingredients:

Aqua, Glycerin, Hydrated Silica, Sorbitol, Silica, Cellulose Gum, Aroma, Xylitol, Cetraria Islandica Extract, Sodium Monofluorophosphate, Sodium Fluoride, Sodium Saccharin, Sodium Myristoyl Sarcosinate, Sodium Methyl Cocoyl Taurate, Sodium Benzoate, Phenoxyethanol, Benzyl Alcohol, Eugenol, Limonene, CI 77891.

PURPOSE

Non-Abrasive Whitening Toothpaste

Advanced Whitening

Cleans, protects and whitens

For daily use

Complete dental care with Arctic Lichen for natural whitening

BlanX Whitening toothpaste containing Arctic Lichen cleans without abrasiveness, restoring the teeth's original whiteness day by day without harming tooth enamel. Arctic Lichen attacks the bacteria that cause plaque, tartar and discolouring of the teeth.

Keep out of reach of children

DOSAGE AND ADMINISTRATION

For daily use

INDICATIONS AND USAGE

For daily use

Warnings